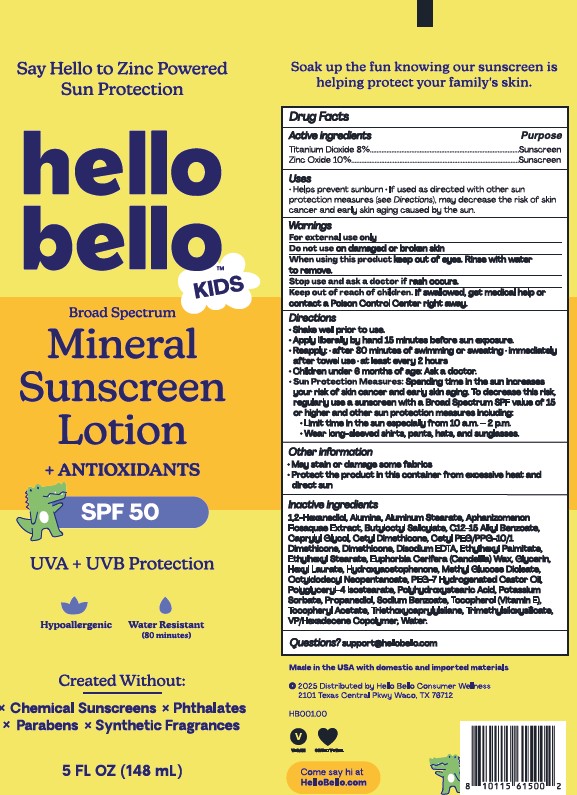 DRUG LABEL: Hello Bello Mineral Sunscreen SPF 50
NDC: 73418-106 | Form: LOTION
Manufacturer: Hello Bello
Category: otc | Type: HUMAN OTC DRUG LABEL
Date: 20250514

ACTIVE INGREDIENTS: ZINC OXIDE 100 mg/1 g; TITANIUM DIOXIDE 80 mg/1 g
INACTIVE INGREDIENTS: PROPANEDIOL; SODIUM BENZOATE; CETYL PEG/PPG-10/1 DIMETHICONE (HLB 5); DIMETHICONE 100; ALUMINUM STEARATE; C12-15 ALKYL BENZOATE; CAPRYLYL GLYCOL; ETHYLHEXYL PALMITATE; OCTYLDODECYL NEOPENTANOATE; TRIETHOXYCAPRYLYLSILANE; POTASSIUM SORBATE; HYDROXYACETOPHENONE; EDETATE DISODIUM; HEXYL LAURATE; POLYGLYCERYL-4 ISOSTEARATE; POLYHYDROXYSTEARIC ACID (2300 MW); WATER; METHYL GLUCOSE DIOLEATE; GLYCERIN; TOCOPHEROL; ETHYLHEXYL STEARATE; .ALPHA.-TOCOPHEROL ACETATE, D-; ALUMINA; VP/HEXADECENE COPOLYMER; EUPHORBIA CERIFERA (CANDELILLA) WAX; PEG-7 HYDROGENATED CASTOR OIL; TRIMETHYLSILOXYSILICATE (M/Q 0.8-1.0); APHANIZOMENON FLOSAQUAE; BUTYLOCTYL SALICYLATE; CETYL DIMETHICONE 25; 1,2-HEXANEDIOL

Mineral Sunscreen Lotion + ANTIOXIDANTS SPF50

Other Information

Protect this product from excessive heat and direct sun

Avoid long-term exposure storage above 40°C (104°F)

May stain some fabrics

Active Ingredients

Titanium Dioxide 8%

Zinc Oxide 10%

Purpose

Sunscreen

Uses

Helps prevent sunburn
If used as directed with other sun protection measures (see Directions), decreases the risk of skin cancer and early skin aging caused by the sun

Directions

Shake well before use

Apply liberally and spread evenly by hand 15 minutes before sun exposure

Reapply:

after 80 minutes of swimming or sweating immediately after towel use
at least every 2 hours

Sun Protection Measures

Spending time in the sun can increase your risk of skin cancer and early skin aging. To decrease this risk, regularly use sunscreen with a Broad Spectrum SPF value of 15 or higher and other sun protection measures including:

Limiting time in the sun, especially from 10a.m. - 2p.m.
Wearing long-sleeved shirts, pants, hats and sunglasses

Children under six months: Ask a doctor

Other Information

Protect this product from excessive heat and direct sun

Avoid long-term exposure storage above 40°C (104°F)

May stain some fabrics

Inactive Ingredients

1,2-Hexanediol, Alumina, Aluminum Stearate, Aphanizomenon Flos-aquae Extract, Butyloctyl Salicylate, C12-15 Alkyl Benzoate, Caprylyl Glycol, Cetyl Dimethicone, Cetyl PEG/PPG-10/1 Dimethicone, Dimethicone, Disodium EDTA, Ethylhexyl Palmitate, Ethylhexyl Stearate, Euphorbia Cerifera (Candelilla) Wax, Glycerin, Hexyl Laurate, Hydroxyacetophenone, Methyl Glucose Dioleate, Octyldodecyl Neopentanoate, PEG-7 Hydrogenated Castor Oil, Polyglyceryl-4 Isostearate, Polyhydroxystearic Acid, Potassium Sorbate, Propanediol, Sodium Benzoate, Tocopherol (Vitamin E), Tocopheryl Acetate, Triethoxycaprylylsilane, Trimethylsiloxysilicate, VP/Hexadecene Copolymer, Water.

Questions?

Support@HelloBello.com